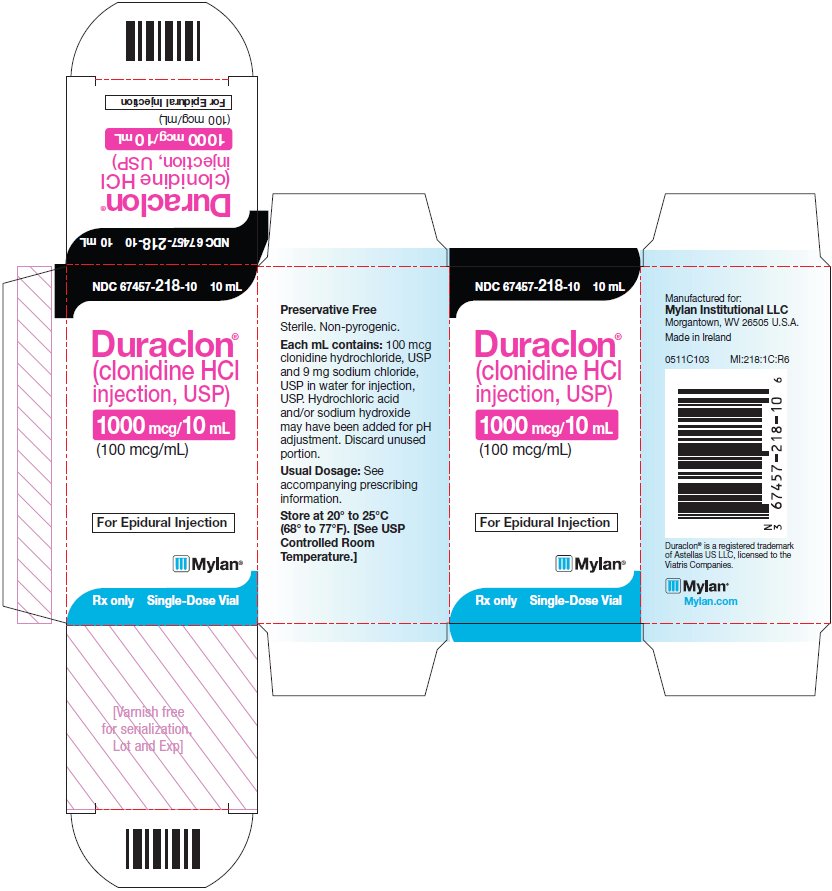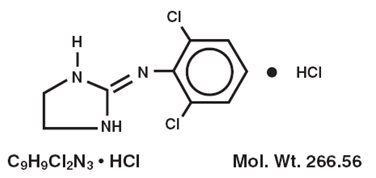 DRUG LABEL: Duraclon
NDC: 67457-218 | Form: INJECTION, SOLUTION
Manufacturer: Mylan Institutional LLC
Category: prescription | Type: HUMAN PRESCRIPTION DRUG LABEL
Date: 20210317

ACTIVE INGREDIENTS: CLONIDINE HYDROCHLORIDE 0.1 mg/1 mL
INACTIVE INGREDIENTS: SODIUM CHLORIDE

BOXED WARNING

NOTE: Duraclon® (epidural clonidine) is not recommended for obstetrical, post-partum, or peri-operative pain management. The risk of hemodynamic instability, especially hypotension and bradycardia, from epidural clonidine may be unacceptable in these patients. However, in a rare obstetrical, post-partum or peri-operative patient, potential benefits may outweigh the possible risks.

DESCRIPTION

Duraclon (clonidine hydrochloride injection, USP) is a centrally-acting analgesic solution for use in continuous epidural infusion devices.

Clonidine Hydrochloride, USP, is an imidazoline derivative and exists as a mesomeric compound. The chemical names are Benzenamine,2,6-dichloro-N-2-imidazolidinylidene-,monohydrochloride and 2-[(2,6-dichlorophenyl)imino]imidazolidine monohydrochloride. The following is the structural formula:

Duraclon (clonidine hydrochloride injection, USP) is supplied as a clear, colorless, preservative-free, pyrogen-free, aqueous sterile solution (pH 5 to 7) in single-dose, 10 mL vials.

Each mL of the 100 mcg/mL (0.1 mg/mL) concentration contains 100 mcg of Clonidine Hydrochloride, USP and 9 mg Sodium Chloride, USP in Water for Injection, USP. Hydrochloric Acid and/or Sodium Hydroxide may have been added for pH adjustment. Each 10 mL vial contains 1 mg (1000 mcg) of clonidine hydrochloride.

CLINICAL PHARMACOLOGY

Mechanism of Action

Epidurally administered clonidine produces dose-dependent analgesia not antagonized by opiate antagonists. The analgesia is limited to the body regions innervated by the spinal segments where analgesic concentrations of clonidine are present. Clonidine is thought to produce analgesia at presynaptic and postjunctional alpha-2-adrenoceptors in the spinal cord by preventing pain signal transmission to the brain.

Pharmacokinetics

Following a 10 minute intravenous infusion of 300 mcg clonidine HCl to five male volunteers, plasma clonidine levels showed an initial rapid distribution phase (mean±SD t^1⁄2=11±9 minutes) followed by a slower elimination phase (t^1⁄2=9±2 hours) over 24 hours. Clonidine’s total body clearance (CL) was 219±92 mL/min.

Following a 700 mcg clonidine HCl epidural dose given over five minutes to four male and five female volunteers, peak clonidine plasma levels (4.4±1.4 ng/mL) were obtained in 19±27 minutes. The plasma elimination half-life was determined to be 22±15 hours following sample collection for 24 hours. CL was 190±70 mL/min. In cerebral spinal fluid (CSF), peak clonidine levels (418±255 ng/mL) were achieved in 26±11 minutes. The clonidine CSF elimination half-life was 1.3±0.5 hours when samples were collected for 6 hours. Compared to men, women had a lower mean plasma clearance, longer mean plasma half-life, and higher mean peak level of clonidine in both plasma and CSF.

In cancer patients who received 14 days of clonidine HCl epidural infusion (rate=30 mcg/hr) plus morphine by patient-controlled analgesia (PCA), steady state clonidine plasma concentrations of 2.2±1.1 and 2.4±1.4 ng/mL were obtained on dosing days 7 and 14, respectively. CL was 279±184 and 272±163 mL/min on these days. CSF concentrations were not determined in these patients.

Distribution

Clonidine is highly lipid soluble and readily distributes into extravascular sites including the central nervous system. Clonidine’s volume of distribution is 2.1±0.4 L/kg. The binding of clonidine to plasma protein is primarily to albumin and varies between 20 and 40% in vitro. Epidurally administered clonidine readily partitions into plasma via the epidural veins and attains systemic concentrations (0.5-2.0 ng/mL) that are associated with a hypotensive effect mediated by the central nervous system.

Excretion

Following an intravenous dose of ^14C-clonidine, 72% of the administered dose was excreted in urine in 96 hours of which 40-50% was unchanged clonidine. Renal clearance for clonidine was determined to be 133±66 mL/min. In a study where ^14C-clonidine was given to subjects with varying degrees of kidney function, elimination half-lives varied (17.5 to 41 hours) as a function of creatinine clearance. In subjects undergoing hemodialysis only 5% of body clonidine stores were removed.

Metabolism

In humans, clonidine metabolism follows minor pathways with the major metabolite, p-hydroxy-clonidine, being present at less than 10% of the concentration of unchanged drug in urine.

Special Populations

The pharmacokinetics of epidurally administered clonidine has not been studied in the pediatric population or in patients with renal or hepatic disease.

Clinical Trials

In a double-blind, randomized study of cancer patients with severe intractable pain below the C4 dermatome not controlled by morphine, 38 patients were randomized to an epidural infusion of Duraclon plus epidural morphine, whereas 47 subjects received epidural placebo plus epidural morphine. Both groups were allowed rescue doses of epidural morphine. Successful analgesia, defined as a decrease in either morphine use or Visual Analog Score (VAS) pain, was significantly more common with epidural clonidine than placebo (45% vs 21%, p=0.016). Only the subgroup of 36 patients with ‘‘neuropathic’’ pain, characterized by the investigator as well-localized, burning, shooting, or electric-like pain in a dermatomal or peripheral nerve distribution had significant analgesic effects relative to placebo in this study.

The most frequent adverse events with clonidine were hypotension (45% vs 11% for placebo, p< 0.001), postural hypotension (32% vs 0%, p< 0.001), dizziness (13% vs 4%, p=0.234), anxiety (11% vs 2%, p=0.168) and dry mouth (13% vs 9%, p=0.505). Both mean blood pressure and heart rate were reduced in the clonidine group. At the conclusion of the two week study period in the clinical trial, all patients were abruptly withdrawn from study drug or placebo. Four patients of the clonidine group suffered rebound hypertension upon withdrawal of clonidine; one of these patients suffered a cerebrovascular accident. Asymptomatic bradycardia was noted in one clonidine patient.

INDICATIONS AND USAGE

Duraclon is indicated in combination with opiates for the treatment of severe pain in cancer patients that is not adequately relieved by opioid analgesics alone. Epidural clonidine is more likely to be effective in patients with neuropathic pain than somatic or visceral pain (see Clinical Trials).

The safety of this drug product has only been established in a highly selected group of cancer patients, and only after an adequate trial of opioid analgesia. Other use is of unproven safety and is not recommended. In a rare patient, the potential benefits may outweigh the known risks (see WARNINGS).

CONTRAINDICATIONS

Duraclon is contraindicated in patients with a history of sensitization or allergic reactions to clonidine. Epidural administration is contraindicated in the presence of an injection site infection, in patients on anticoagulant therapy, and in those with a bleeding diathesis. Administration of Duraclon above the C4 dermatome is contraindicated since there are no adequate safety data to support such use (see WARNINGS).

WARNINGS

Use in Postoperative or Obstetrical Analgesia

Duraclon (epidural clonidine) is not recommended for obstetrical, post-partum, or peri-operative pain management. The risk of hemodynamic instability, especially hypotension and bradycardia, from epidural clonidine may be unacceptable in these patients.

Hypotension

Because severe hypotension may follow the administration of clonidine, it should be used with caution in all patients. It is not recommended in most patients with severe cardiovascular disease or in those who are otherwise hemodynamically unstable. The benefit of its administration in these patients should be carefully balanced against the potential risks resulting from hypotension.

Vital signs should be monitored frequently, especially during the first few days of epidural clonidine therapy. When clonidine is infused into the upper thoracic spinal segments, more pronounced decreases in the blood pressure may be seen.

Clonidine decreases sympathetic outflow from the central nervous system resulting in decreases in peripheral resistance, renal vascular resistance, heart rate, and blood pressure. However, in the absence of profound hypotension, renal blood flow and glomerular filtration rate remain essentially unchanged.

In the pivotal double-blind, randomized study of cancer patients, where 38 subjects were administered epidural Duraclon at 30 mcg/hr in addition to epidural morphine, hypotension occurred in 45% of subjects. Most episodes of hypotension occurred within the first four days after beginning epidural clonidine. However, hypotensive episodes occurred throughout the duration of the trial. There was a tendency for these episodes to occur more commonly in women, and in those with higher serum clonidine levels. Patients experiencing hypotension also tended to weigh less than those who did not experience hypotension. The hypotension is usually responsive to intravenous fluids and, if necessary, appropriate parenterally-administered pressor agents.

Published reports on the use of epidural clonidine for intraoperative or postoperative analgesia also show a consistent and marked hypotensive response to clonidine. Severe hypotension may occur even if intravenous fluid pretreatment is given.

Withdrawal

Sudden cessation of clonidine treatment, regardless of the route of administration, has, in some cases, resulted in symptoms such as nervousness, agitation, headache, and tremor, accompanied or followed by a rapid rise in blood pressure. The likelihood of such reactions appears to be greater after administration of higher doses or with concomitant beta-blocker treatment. Special caution is therefore advised in these situations. Rare instances of hypertensive encephalopathy, cerebrovascular accidents and death have been reported after abrupt clonidine withdrawal. Patients with a history of hypertension and/or other underlying cardiovascular conditions may be at particular risk of the consequences of abrupt discontinuation of clonidine. In the pivotal double-blind, randomized cancer pain study, four of 38 subjects receiving 720 mcg of clonidine per day experienced rebound hypertension following abrupt withdrawal. One of these patients with rebound hypertension subsequently experienced a cerebrovascular accident.

Careful monitoring of infusion pump function and inspection of catheter tubing for obstruction or dislodgement can help reduce the risk of inadvertent abrupt withdrawal of epidural clonidine. Patients should notify their physician immediately if clonidine administration is inadvertently interrupted for any reason. Patients should also be instructed not to discontinue therapy without consulting their physician.

When discontinuing therapy with epidural clonidine, the physician should reduce the dose gradually over 2 to 4 days to avoid withdrawal symptoms.

An excessive rise in blood pressure following discontinuation of epidural clonidine can be treated by administration of clonidine or by intravenous phentolamine. If therapy is to be discontinued in patients receiving a beta-blocker and clonidine concurrently, the beta-blocker should be withdrawn several days before the gradual discontinuation of epidural clonidine.

Infections

Infections related to implantable epidural catheters pose a serious risk. Evaluation of fever in a patient receiving epidural clonidine should include the possibility of a catheter-related infection such as meningitis or epidural abscess.

PRECAUTIONS

General

Cardiac Effects: Epidural clonidine frequently causes decreases in heart rate. Symptomatic bradycardia can be treated with atropine. Rarely, atrioventricular block greater than first degree has been reported. Clonidine does not alter the hemodynamic response to exercise, but may mask the increase in heart rate associated with hypovolemia.

Respiratory Depression and Sedation: Clonidine administration may result in sedation through the activation of alpha-adrenoceptors in the brainstem. High doses of clonidine cause sedation and ventilatory abnormalities that are usually mild. Tolerance to these effects can develop with chronic administration. These effects have been reported with bolus doses that are significantly larger than the infusion rate recommended for treating cancer pain.

Depression: Depression has been seen in a small percentage of patients treated with oral or transdermal clonidine. Depression commonly occurs in cancer patients and may be exacerbated by treatment with clonidine. Patients, especially those with a known history of affective disorders, should be monitored for the signs and symptoms of depression.

Pain of Visceral or Somatic Origin: In the clinical investigations, at doses tested, Duraclon was most effective in well-localized, ‘‘neuropathic’’ pain that was characterized as electrical, burning, or shooting in nature, and which was localized to a dermatomal or peripheral nerve distribution. Duraclon may be less effective, or possibly ineffective in the treatment of pain that is diffuse, poorly localized, or visceral in origin.

Information for Patients

Patients should be instructed about the risks of rebound hypertension and warned not to discontinue clonidine except under the supervision of a physician. Patients should notify their physician immediately if clonidine administration is inadvertently interrupted for any reason. Patients who engage in potentially hazardous activities, such as operating machinery or driving, should be advised of the potential sedative and hypotensive effects of epidural clonidine. They should also be informed that sedative effects may be increased by CNS-depressing drugs such as alcohol and barbiturates, and that hypotensive effects may be increased by opiates.

Drug Interactions

Clonidine may potentiate the CNS-depressive effect of alcohol, barbiturates or other sedating drugs. Narcotic analgesics may potentiate the hypotensive effects of clonidine. Tricyclic anti-depressants may antagonize the hypotensive effects of clonidine. The effects of tricyclic anti-depressants on clonidine’s analgesic actions are not known.

Beta-blockers may exacerbate the hypertensive response seen with clonidine withdrawal. Also, due to the potential for additive effects such as bradycardia and AV block, caution is warranted in patients receiving clonidine with agents known to affect sinus node function or AV nodal conduction, e.g., digitalis, calcium channel blockers, and beta-blockers.

There is one reported case of a patient with acute delirium associated with the simultaneous use of fluphenazine and oral clonidine. Symptoms resolved when clonidine was withdrawn and recurred when the patient was rechallenged with clonidine.

Epidural clonidine may prolong the duration of pharmacologic effects of epidural local anesthetics, including both sensory and motor blockade.

Carcinogenesis, Mutagenesis, Impairment of Fertility

In a 132-week study in rats, clonidine hydrochloride administered as a dietary admixture at 5-8 times (based on body surface area) the 50 mcg/kg maximum recommended daily human dose (MRDHD) for hypertension did not show any carcinogenic potential. Clonidine was inactive in the Ames test of mutagenicity. Fertility of male or female rats was unaffected by oral clonidine hydrochloride doses as high as 150 mcg/kg, or about 0.5 times the MRDHD. Fertility of female rats did, however, appear to be affected in another experiment at oral dose levels of 500-2000 mcg/kg, or 2-7 times the MRDHD.

Usage in Pregnancy/Teratogenic Effects

Reproduction studies in rabbits at clonidine hydrochloride doses up to approximately the MRDHD revealed no evidence of teratogenic or embryotoxic potential. In rats, however, doses as low as one-third the MRDHD were associated with increased resorptions in a study in which dams were treated continuously from 2 months prior to mating. Increased resorptions were not associated with treatment with the same or higher doses up to 0.5 times the MRDHD when dams were treated on days 6-15 of gestation. Increased resorptions were observed at higher levels (7-times the MRDHD) in rats and mice treated on days 1-14 of gestation.

Clonidine readily crosses the placenta and its concentrations are equal in maternal and umbilical cord plasma; amniotic fluid concentrations can be 4-times those found in serum. There are no adequate and well-controlled studies in pregnant women during early gestation when organ formation takes place. Studies using epidural clonidine during labor have demonstrated no apparent adverse effects on the infant at the time of delivery. However, these studies did not monitor the infants for hemodynamic effects in the days following delivery. Clonidine hydrochloride injection should be used during pregnancy only if the potential benefits justify the potential risk to the fetus.

Labor and Delivery

There are no adequate controlled clinical trials evaluating the safety, efficacy, and dosing of Duraclon in obstetrical settings. Because maternal perfusion of the placenta is critically dependent on blood pressure, use of Duraclon as an analgesic during labor and delivery is not indicated (see WARNINGS).

Nursing Mothers

Concentrations of clonidine in human breast milk are approximately twice those found in maternal plasma. Caution should be exercised when clonidine is administered to a nursing woman. Because of the potential for severe adverse reactions in nursing infants, a decision should be made to either discontinue nursing or to discontinue clonidine.

Pediatric Use

The safety and effectiveness of Duraclon in this limited indication and clinical population have been established in patients old enough to tolerate placement and management of an epidural catheter, based on evidence from adequate and well controlled studies in adults and experience with the use of clonidine in the pediatric age group for other indications. The use of Duraclon should be restricted to pediatric patients with severe intractable pain from malignancy that is unresponsive to epidural or spinal opiates or other more conventional analgesic techniques. The starting dose of Duraclon should be selected on per kilogram basis (0.5 mcg per kg per hour) and cautiously adjusted based on the clinical response.

ADVERSE REACTIONS

Adverse reactions seen during continuous epidural clonidine infusion are dose-dependent and typical for a compound of this pharmacologic class. The adverse events most frequently reported in the pivotal controlled clinical trial of continuous epidural clonidine administration consisted of hypotension, postural hypotension, decreased heart rate, rebound hypertension, dry mouth, nausea, confusion, dizziness, somnolence, and fever. Hypotension is the adverse event that most frequently requires treatment. The hypotension is usually responsive to intravenous fluids and, if necessary, appropriate parenterally-administered pressor agents. Hypotension was observed more frequently in women and in lower weight patients, but no dose-related response was established.

Implantable epidural catheters are associated with a risk of catheter-related infections, including meningitis and/or epidural abscess. The risk depends on the clinical situation and the type of catheter used, but catheter related infections occur in 5%-20% of patients, depending on the kind of catheter used, catheter placement technique, quality of catheter care, and length of catheter placement.

The inadvertent intrathecal administration of clonidine has not been associated with a significantly increased risk of adverse events, but there are inadequate safety and efficacy data to support the use of intrathecal clonidine.

Epidural clonidine was compared to placebo in a two week double-blind study of 85 terminal cancer patients with intractable pain receiving epidural morphine. The following adverse events were reported in two or more patients and may be related to administration of either Duraclon or morphine.

Incidence of Adverse Events in the Two-Week Trial
Adverse Events | Clonidine; N = 38; n (%) | Placebo; N = 47; n (%)
Total Number of Patients Who Experienced at Least One Adverse Event | 37 (97.4) | 38 (80.5)
Hypotension | 17 (44.8) | 5 (10.6)
Postural Hypotension | 12 (31.6) | 0 (0)
Dry Mouth | 5 (13.2) | 4 (8.5)
Nausea | 5 (13.2) | 10 (21.3)
Somnolence | 5 (13.2) | 10 (21.3)
Dizziness | 5 (13.2) | 2 (4.3)
Confusion | 5 (13.2) | 5 (10.6)
Vomiting | 4 (10.5) | 7 (14.9)
Nausea/Vomiting | 3 (7.9) | 1 (2.1)
Sweating | 2 (5.3) | 0 (0)
Chest Pain | 2 (5.3) | 0 (0)
Hallucination | 2 (5.3) | 1 (2.1)
Tinnitus | 2 (5.3) | 0 (0)
Constipation | 1 (2.6) | 2 (4.3)
Tachycardia | 1 (2.6) | 2 (4.3)
Hypoventilation | 1 (2.6) | 2 (4.3)

An open label long-term extension of the above trial was performed. Thirty-two subjects received epidural clonidine and morphine for up to 94 weeks with a median dosing period of 10 weeks. The following adverse events (and percent incidence) were reported: hypotension/postural hypotension (47%); nausea (13%); anxiety/confusion (38%); somnolence (25%); urinary tract infection (22%); constipation, dyspnea, fever, infection (6% each); asthenia, hyperaesthesia, pain, skin ulcer, and vomiting (5% each). Eighteen percent of subjects discontinued this study as a result of catheter-related problems (infections, accidental dislodging, etc.), and one subject developed meningitis, possibly as a result of a catheter-related infection. In this study, rebound hypertension was not assessed, and ECG and laboratory data were not systematically sought.

The following adverse reactions have also been reported with the use of any dosage form of clonidine. In many cases patients were receiving concomitant medication and a causal relationship has not been established:

Body as a Whole: Weakness, 10%; fatigue, 4%; headache and withdrawal syndrome, each 1%. Also reported were pallor, a weakly positive Coomb’s test, and increased sensitivity to alcohol.

Cardiovascular: Palpitations and tachycardia, and bradycardia, each 0.5%. Syncope, Raynaud’s phenomenon, congestive heart failure, and electrocardiographic abnormalities (i.e., sinus node arrest, functional bradycardia, high degree AV block) have been reported rarely. Rare cases of sinus bradycardia and atrioventricular block have been reported, both with and without the use of concomitant digitalis.

Central Nervous System: Nervousness and agitation, 3%; mental depression, 1%; insomnia, 0.5%. Cerebrovascular accidents, other behavioral changes, vivid dreams or nightmares, restlessness, and delirium have been reported rarely.

Dermatological: Rash, 1%; pruritus, 0.7%; hives, angioneurotic edema and urticaria, 0.5%; alopecia, 0.2%.

Gastrointestinal: Anorexia and malaise, each 1%; mild transient abnormalities in liver function tests, 1%; hepatitis, parotitis, ileus and pseudo obstruction, and abdominal pain, rarely.

Genitourinary: Decreased sexual activity, impotence, and libido, 3%; nocturia, about 1%; difficulty in micturition, about 0.2%; urinary retention, about 0.1%.

Hematologic: Thrombocytopenia, rarely.

Metabolic: Weight gain, 0.1%; gynecomastia, 1%; transient elevation of glucose or serum phosphatase, rarely.

Musculoskeletal: Muscle or joint pain, about 0.6%; leg cramps, 0.3%.

Oro-otolaryngeal: Dryness of the nasal mucosa was rarely reported.

Ophthalmological: Dryness of the eyes, burning of the eyes and blurred vision were rarely reported.

OVERDOSAGE

Hypertension may develop early and may be followed by hypotension, bradycardia, respiratory depression, hypothermia, drowsiness, decreased or absent reflexes, irritability, and miosis. With large oral overdoses, reversible cardiac conduction defects or arrhythmias, apnea, coma, and seizures have been reported. As little as 100 mcg of oral clonidine has produced signs of toxicity in pediatric patients.

There is no specific antidote for clonidine overdosage. Supportive care may include atropine sulfate for bradycardia, intravenous fluids and/or vasopressor agents for hypotension. Hypertension associated with overdosage has been treated with intravenous furosemide, diazoxide or alpha-blocking agents such as phentolamine. Naloxone may be a useful adjunct in the treatment of clonidine induced respiratory depression, hypotension, and/or coma; blood pressure should be monitored since the administration of naloxone has occasionally resulted in paradoxical hypertension. Tolazoline administration has yielded inconsistent results and is not recommended as first-line therapy. Dialysis is not likely to significantly enhance the elimination of clonidine.

The largest overdose reported to date involved a 28-year old white male who ingested 100 mg of clonidine hydrochloride powder. This patient developed hypertension followed by hypotension, bradycardia, apnea, hallucinations, semi-coma, and premature ventricular contractions. The patient fully recovered after intensive treatment. Plasma clonidine levels were 60 ng/mL after 1 hour, 190 ng/mL after 1.5 hours, 370 ng/mL after 2 hours, and 120 ng/mL after 5.5 and 6.5 hours. In mice and rats, the oral LD50 of clonidine is 206 and 465 mg/kg, respectively.

DOSAGE AND ADMINISTRATION

The recommended starting dose of Duraclon for continuous epidural infusion is 30 mcg/hr. Although dosage may be titrated up or down depending on pain relief and occurrence of adverse events, experience with dosage rates above 40 mcg/hr is limited.

Familiarization with the continuous epidural infusion device is essential. Patients receiving epidural clonidine from a continuous infusion device should be closely monitored for the first few days to assess their response.

Renal Impairment

Dosage should be adjusted according to the degree of renal impairment, and patients should be carefully monitored. Since only a minimal amount of clonidine is removed during routine hemodialysis, there is no need to give supplemental clonidine following dialysis.

Duraclon must not be used with a preservative.

Parenteral drug products should be inspected visually for particulate matter and discoloration prior to administration, whenever solution and container permit.

Discard unused portion.

HOW SUPPLIED

NDC 67457-218-10, 100 mcg/mL solution in
10 mL vials, packaged individually.

Store at 20° to 25°C (68° to 77°F). [See USP Controlled Room Temperature.]

Preservative Free. Discard unused portion.

Duraclon® is a registered trademark of Astellas US LLC, licensed to the Viatris Companies.

Manufactured for:
Mylan Institutional LLC
Morgantown, WV 26505 U.S.A.

Manufactured by:
Mylan Institutional
Galway, Ireland

0919L103

Revised: 3/2021
MI:DURAIJ:R6

To request medical information or to report suspected adverse reactions, contact Drug Safety at 1-877-446-3679 (1-877-4-INFO-RX) or FDA at 1-800-FDA-1088 or www.fda.gov/medwatch.

PRINCIPAL DISPLAY PANEL – 100 mcg/mL

NDC 67457-218-10 10 mL

Duraclon®
(clonidine HCl
injection, USP)

1000 mcg/10 mL
(100 mcg/mL)

For Epidural Injection

Rx only Single-Dose Vial

Preservative Free

Sterile. Non-pyrogenic.

Each mL contains: 100 mcg
clonidine hydrochloride, USP
and 9 mg sodium chloride, USP
in water for injection, USP.

Hydrochloric acid and/or sodium
hydroxide may have been added
for pH adjustment. Discard
unused portion.

Usual Dosage: See
accompanying prescribing
information.

Store at 20° to 25°C (68° to
77°F). [See USP Controlled
Room Temperature.]

Manufactured for:
Mylan Institutional LLC
Morgantown, WV 26505 U.S.A.

Made in Ireland

0511C103 MI:218:1C:R6

Duraclon® is a registered trademark of Astellas US LLC, licensed to the Viatris Companies..

Mylan.com